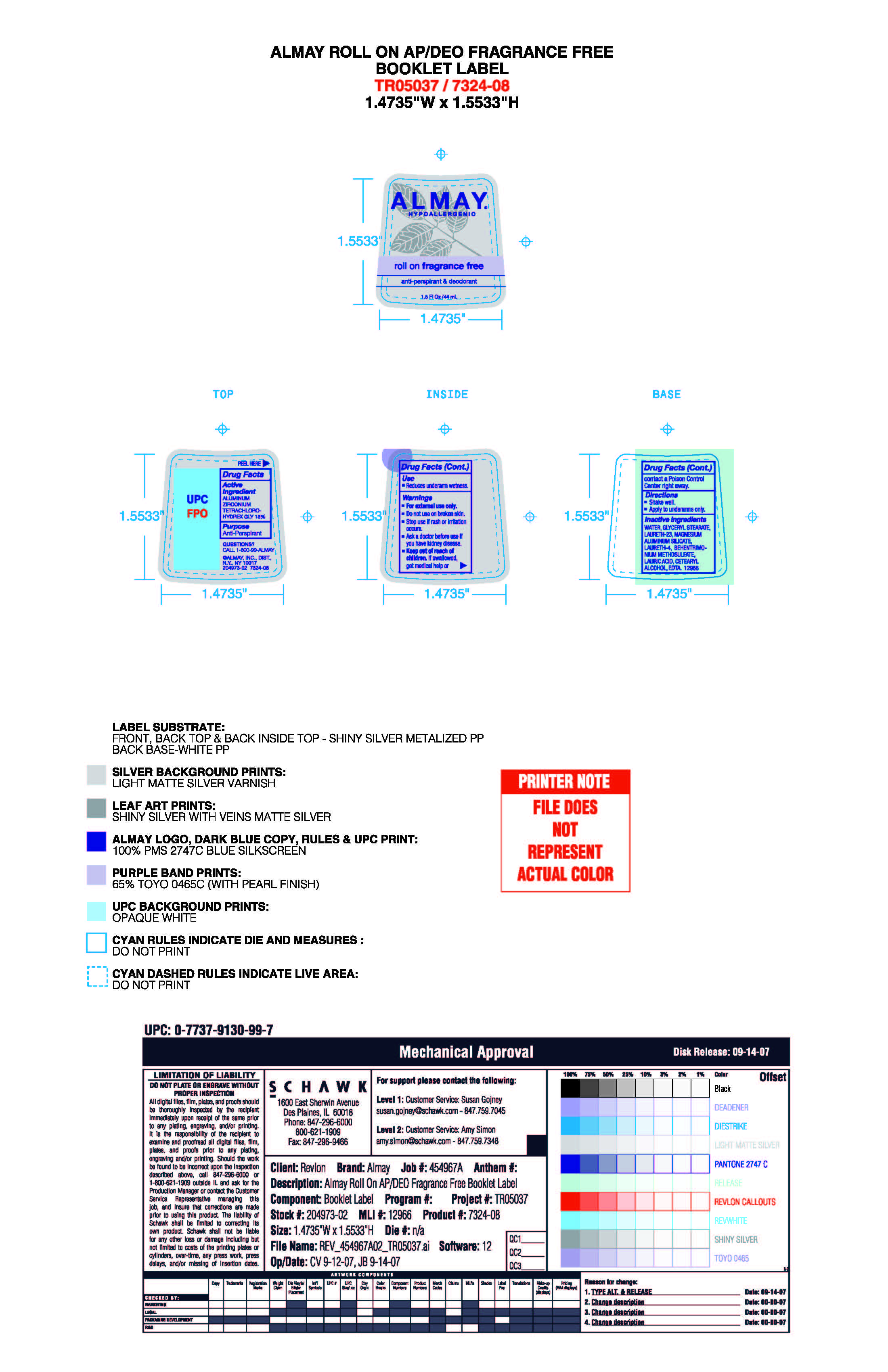 DRUG LABEL: Almay Roll-On For Sensitive Skin - Fragrance-Free
NDC: 0311-0714 | Form: LIQUID
Manufacturer: Almay, Inc.
Category: otc | Type: HUMAN OTC DRUG LABEL
Date: 20241230

ACTIVE INGREDIENTS: ALUMINUM SESQUICHLOROHYDRATE 0.25 g/1 mL
INACTIVE INGREDIENTS: EDTA; BEHENTRIMONIUM METHOSULFATE; GLYCERYL STEARATE SE; WATER; DI-PPG-2 MYRETH-10 ADIPATE; LAURETH-23; MAGNESIUM ALUMINUM SILICATE; LAURETH-4; POLYSORBATE 20; LAURIC ACID

Almay Roll-On For Sensitive Skin - Fragrance-Free

ACTIVE INGREDIENT

Aluminum Sesquicholorhydrate 25%

Purpose

Antiperspirant

Warnings:

For external use only.

Do not use on broken skin

Ask a doctor before use if you have kidney disease

Stop use if rash or irriation occurs

KEEP OUT OF REACH OF CHILDREN

If swallowed, get medical help or contact a Poison Control Center right away.

Inactive Ingredients

AQUA ((WATER) EAU), DI-PPG-2 MYRETH-10 ADIPATE, LAURETH-23, GLYCERYL STEARATE, MAGNESIUM ALUMINUM SILICATE, LAURETH-4, POLYSORBATE 20, LAURIC ACID, CETEARYL ALCOHOL, BENHENTRIMONIUM METHOSULFATE, EDTA

INDICATIONS AND USAGE

Reduces underarm wetness